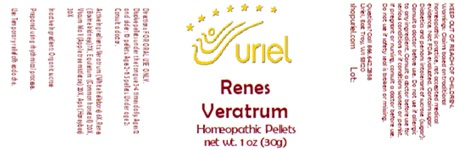 DRUG LABEL: Renes Veratrum
NDC: 48951-8133 | Form: PELLET
Manufacturer: Uriel Pharmacy Inc.
Category: homeopathic | Type: HUMAN OTC DRUG LABEL
Date: 20250916

ACTIVE INGREDIENTS: VERATRUM ALBUM ROOT 6 [hp_X]/1 1; PORK KIDNEY 7 [hp_X]/1 1; EQUISETUM ARVENSE TOP 20 [hp_X]/1 1; VISCUM ALBUM FRUITING TOP 20 [hp_X]/1 1; APIS MELLIFERA 30 [hp_X]/1 1
INACTIVE INGREDIENTS: SUCROSE

Renes Veratrum

INDICATIONS AND USAGE

Directions: FOR ORAL USE ONLY.

DOSAGE AND ADMINISTRATION

Dissolve pellets under the tongue 3-4 times daily. Ages 12 and older: 10 pellets. Ages 2-11: 5 pellets. Under age 2: Consult a doctor.

ACTIVE INGREDIENT

Active Ingredients: Veratrum (White hellebore) 6X, Renes (Bovine kidneys) 7X, Equisetum (Common horsetail) 20X, Viscum Mali (Apple tree mistletoe) 20X, Apis (Honeybee) 30X

Inactive Ingredient: Organic sucrose

Prepared using rhythmical processes.

PURPOSE

Use: Temporary relief of headache.

KEEP OUT OF REACH OF CHILDREN.

WARNINGS

Warnings: Claims based on traditional homeopathic practice, not accepted medical evidence. Not FDA evaluated. Contains sugar. Diabetics and persons intolerant of sucrose (sugar): Consult a doctor before use. Do not useif allergic to any ingredient. Consult a doctor before use for serious conditions or if conditions worsen or persist. If pregnant or nursing, consult a doctor before use. Do not use if safety seal is broken or missing.

QUESTIONS

Questions? Call 866.642.2858 Uriel, East Troy, WI 53120 www.urielpharmacy.com